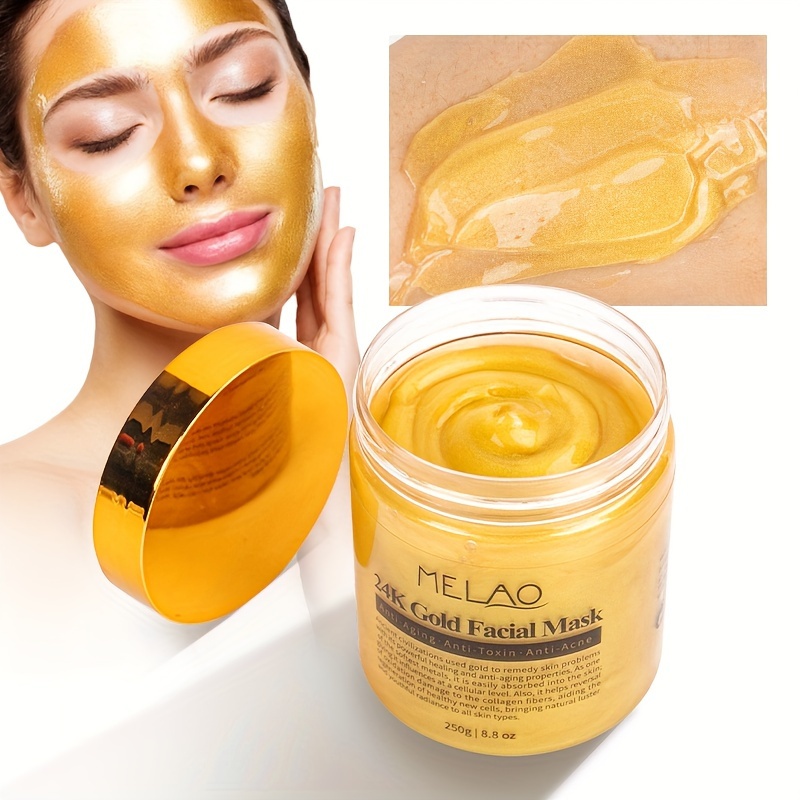 DRUG LABEL: MELAO 24K Gold Facial Mask
NDC: 83566-577 | Form: STICK
Manufacturer: Guangzhou Yilong Cosmetics Co., Ltd
Category: otc | Type: HUMAN OTC DRUG LABEL
Date: 20240809

ACTIVE INGREDIENTS: ALLANTOIN 6 g/100 g; CENTELLA ASIATICA 3 g/100 g
INACTIVE INGREDIENTS: .IOTA.-CARRAGEENAN SODIUM 10 g/100 g; WATER 50 g/100 g; HYDROLYZED WHEAT PROTEIN (ENZYMATIC, 3000 MW) 10 g/100 g; AMINO ACIDS, MILK 8 g/100 g; .ALPHA.-TOCOPHEROL ACETATE 6 g/100 g; ARNICA MONTANA FLOWER WATER 0.5 g/100 g; POLYGLUTAMIC ACID (1200 MW) 0.3 g/100 g

MELAO 24K Gold Facial Mask 250g

Active ingredients

Allantoin 6%

Centella Asiatica Extract 3%

Inactive ingredients

Sodium Hyaluronate 10%

water 50%

Hydrolyzed Collagen 10%

Silk Amino Acids 8%

Tocopherol/Wheat Polyepptides 6%

Arnica Montana Flower Extract 0.5%

Xanthan Gum 0.5%

Codium Tomentosum Extract 0.5%

Polyglutamic Aicd 0.3%

Cereus Grandiflorus(Cactus)Extract 0.1%

Portulaca Oleracer Extract 0.05%

Leontopodium Alpinum Extract 0.03%

Gold 0.02%

Butyl Glycolate 5%

Purpose

Moisture

Uses

Step 1: Clean and thoroughly dry your skin.
Step 2: Turn off the cover and apply the facial mask evenly on the face. The thickness should cover the original skin color
Step 3: Let it stand for 10-15 minutes, then rinse with clean water

Warning

For external use only.

Stop use and ask a doctor if

.rash occurs.

.Do not use

on damaged or broken skin.

When using this product

keep out of eyes. Rinse withwater to remove.

Keep out of reach of children.

If swallowed, get medical help or contact a Poison Control Center right away.

DOSAGE & ADMINISTRATION

Squeeze out an appropriate amount of sunscreen and spread evenly on skin.